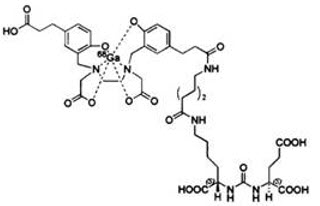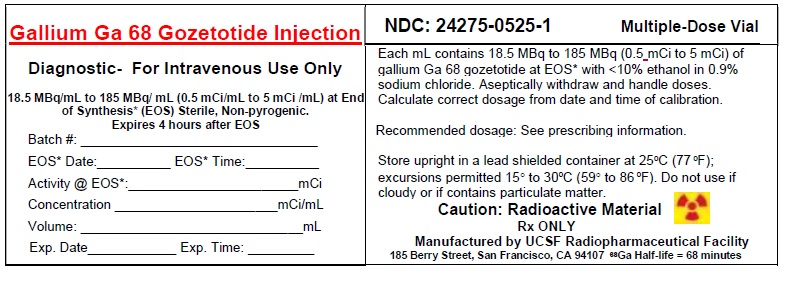 DRUG LABEL: Gallium Ga-68 PSMA-11
NDC: 24275-0525 | Form: INJECTION, SOLUTION
Manufacturer: UCSF Radiopharmaceutical Facility
Category: prescription | Type: HUMAN PRESCRIPTION DRUG LABEL
Date: 20251114

ACTIVE INGREDIENTS: GALLIUM GA-68 GOZETOTIDE 5 mCi/1 mL
INACTIVE INGREDIENTS: ALCOHOL; SODIUM CHLORIDE

HIGHLIGHTS OF PRESCRIBING INFORMATION

These highlights do not include all the information needed to use GALLIUM GA 68 GOZETOTIDE§ Injection safely and effectively. See full prescribing information for GALLIUM GA 68 GOZETOTIDE INJECTION.
GALLIUM GA 68 GOZETOTIDE Injection, for intravenous use
Initial U.S. Approval: 2020(§Gozetotide is also known as PSMA-11)

1 INDICATIONS AND USAGE

Gallium Ga 68 Gozetotide Injection is a radioactive diagnostic agent indicated for positron emission tomography (PET) of prostate-specific membrane antigen (PSMA) positive lesions in men with prostate cancer:

- with suspected metastasis who are candidates for initial definitive therapy.
- with suspected recurrence based on elevated serum prostate-specific antigen (PSA) level. (1)

2 DOSAGE AND ADMINISTRATION

- Use appropriate aseptic technique and radiation safety handling measures to maintain sterility during all operations involved in the manipulation and administration of Gallium Ga 68 Gozetotide Injection. (2.1)
- The recommended adult dose is 111 MBq to 259 MBq (3 mCi to 7 mCi) as a bolus intravenous injection. (2.2)
- A diuretic expected to act within the uptake time period may be administered at the time of radiotracer injection. (2.2)
- Initiate imaging 50 to 100 minutes after administration. The patient should void immediately prior to initiation of imaging. Scan should begin caudally and proceed cranially. (2.4)
- See full prescribing information for additional preparation, administration, imaging, and radiation dosimetry information. (2)

3 DOSAGE FORMS AND STRENGTHS

Injection: clear, colorless solution in a multiple-dose vial containing 18.5 MBq/mL to 185 MBq/mL (0.5 mCi/mL to 5 mCi/mL) Gallium Ga 68 Gozetotide at calibration time (3)

4 CONTRAINDICATIONS

None (4)

5 WARNINGS AND PRECAUTIONS

- Risk for misdiagnosis: Gallium Ga 68 gozetotide uptake can be seen in a variety of tumor types and in non-malignant processes. Image interpretation errors can occur with gallium Ga 68 gozetotide PET. (5.1)
- Radiation risk: Ensure safe handling to protect patients and health care workers from unintentional radiation exposure. (2.1, 5.2)

6 ADVERSE REACTIONS

The most commonly reported adverse reactions include nausea, diarrhea, and dizziness. (6)

To report SUSPECTED ADVERSE REACTIONS, contact UCSF Nuclear Medicine at 1-888-919-0740 or FDA at 1-800-FDA-1088 or www.fda.gov/medwatch.

.

FULL PRESCRIBING INFORMATION

1 INDICATIONS AND USAGE

Gallium Ga 68 Gozeotide Injection is indicated for positron emission tomography (PET) of prostate-specific membrane antigen (PSMA) positive lesions in men with prostate cancer:

- with suspected metastasis who are candidates for initial definitive therapy.
- with suspected recurrence based on elevated serum prostate-specific antigen (PSA) level.

2 DOSAGE AND ADMINISTRATION

2.1 Radiation Safety – Drug Handling

Handle Gallium Ga 68 Gozetotide Injection with appropriate safety measures to minimize radiation exposure [see Warnings and Precautions (5.2)] . Use waterproof gloves, effective radiation shielding, and other appropriate safety measures when preparing and handling Gallium Ga 68 Gozetotide Injection.

Radiopharmaceuticals should be used by or under the control of physicians who are qualified by specific training and experience in the safe use and handling of radionuclides, and whose experience and training have been approved by the appropriate governmental agency authorized to license the use of radionuclides.

2.2 Recommended Dosage and Administration Instructions

Recommended Dosage

In adults, the recommended amount of radioactivity to be administered for PET is 111 MBq to 259 MBq (3 mCi to 7 mCi) administered as an intravenous bolus injection.

Administration

- Use aseptic technique and radiation shielding when withdrawing and administering Gallium Ga 68 Gozetotide Injection.
- Calculate the necessary volume to administer based on calibration time and required dose.
- Inspect Gallium Ga 68 Gozetotide Injection visually for particulate matter and discoloration before administration. Do not use the drug if the solution contains particulate matter or is discolored.
- Gallium Ga 68 Gozetotide Injection may be diluted with sterile 0.9% Sodium Chloride Injection, USP.
- Assay the final dose immediately before administration to the patient in a dose calibrator.
- After injection of Gallium Ga 68 Gozeotide Injection, administer an intravenous flush of sterile 0.9% Sodium Chloride Injection, USP to ensure full delivery of the dose.
- Dispose of any unused drug in a safe manner in compliance with applicable regulations.
- Unless contraindicated, a diuretic expected to act within the uptake time period may be administered at the time of radiotracer injection to potentially decrease artifact from radiotracer accumulation in the urinary bladder and ureters.

2.3 Patient Preparation Prior to PET Imaging

Instruct patients to drink a sufficient amount of water to ensure adequate hydration prior to administration of Gallium Ga 68 Gozeotide Injection and to continue to drink and void frequently following administration to reduce radiation exposure, particularly during the first hour after administration [see Warnings and Precautions (5.2)] .

2.4 Image Acquisition

Position the patient supine with arms above the head. Begin PET scanning 50 to 100 minutes after the intravenous administration of Gallium Ga 68 Gozetotide Injection. Patients should void immediately prior to image acquisition and that image acquisition should begin at the proximal thighs and proceed cranially to the skull base or skull vertex. Adapt imaging technique according to the equipment used and patient characteristics in order to obtain the best image quality possible.

2.5 Image Interpretation

Gallium Ga 68 Gozetotide binds to prostate-specific membrane antigen (PSMA). Based on the intensity of the signals, PET images obtained using Gallium Ga 68 Gozetotide Injection indicate the presence of PSMA in tissues. Lesions should be considered suspicious if uptake is greater than physiologic uptake in that tissue or greater than adjacent background if no physiologic uptake is expected. Tumors that do not bear PSMA will not be visualized. Increased uptake in tumors is not specific for prostate cancer [see Warnings and Precautions (5.1)] .

2.6 Radiation Dosimetry

Estimated radiation absorbed doses per injected activity for organs and tissues of adult male patients following an intravenous bolus of Gallium Ga 68 Gozetotide Injection are shown in Table 1.

The effective radiation dose resulting from the administration of 259 MBq (7 mCi) is about 4.4 mSv. The radiation doses for this administered dose to the critical organs, which are the kidneys, urinary bladder, and spleen, are 96.2 mGy, 25.4 mGy, and 16.8 mGy, respectively.

These radiation doses are for Gallium Ga 68 Gozetotide Injection alone. If CT or a transmission source are used for attenuation correction, the radiation dose will increase by an amount that varies by technique.

Table 1: Estimated Radiation Absorbed Dose per Injected Activity in Selected Organs and Tissues of Adults after Intravenous Administration of Gallium Ga 68 Gozetotide Injection
Organ | Absorbed dose (mGy/MBq)
Organ | Mean | SD
Adrenals | 0.0156 | 0.0014
Brain | 0.0104 | 0.0011
Breasts | 0.0103 | 0.0011
Gallbladder | 0.0157 | 0.0012
Lower Colon | 0.0134 | 0.0009
Small Intestine | 0.0140 | 0.0020
Stomach | 0.0129 | 0.0008
Heart | 0.0120 | 0.0009
Kidneys | 0.3714 | 0.0922
Liver | 0.0409 | 0.0076
Lungs | 0.0111 | 0.0007
Muscle | 0.0103 | 0.0003
Pancreas | 0.0147 | 0.0009
Red Marrow | 0.0114 | 0.0016
Skin | 0.0091 | 0.0003
Spleen | 0.0650 | 0.0180
Testes | 0.0111 | 0.0006
Thymus | 0.0105 | 0.0006
Thyroid | 0.0104 | 0.0006
Urinary Bladder | 0.0982 | 0.0286
Total Body | 0.0143 | 0.0013
Effective Dose (mSv/MBq) | 0.0169 | 0.0015

3 DOSAGE FORMS AND STRENGTHS

Injection: supplied as a clear, colorless solution in a 20 mL multiple-dose vial containing 18.5 MBq/mL to 185 MBq/mL (0.5 mCi/mL to 5 mCi/mL) of Gallium Ga 68 Gozetotide at calibration time.

4 CONTRAINDICATIONS

None

5 WARNINGS AND PRECAUTIONS

5.1 Risk for Misdiagnosis

Image interpretation errors can occur with gallium Ga 68 gozetotide PET. A negative image does not rule out the presence of prostate cancer and a positive image does not confirm the presence of prostate cancer. The performance of Gallium Ga 68 Gozetotide Injection for imaging of biochemically recurrent prostate cancer seems to be affected by serum PSA levels and by site of disease [See Clinical Studies (14)] . The performance of Gallium Ga 68 Gozetotide Injection for imaging of metastatic pelvic lymph nodes prior to initial definitive therapy seems to be affected by Gleason score [See Clinical Studies (14)] . Gallium Ga 68 Gozetotide uptake is not specific for prostate cancer and may occur with other types of cancer as well as non-malignant processes such as Paget's disease, fibrous dysplasia, and osteophytosis. Clinical correlation, which may include histopathological evaluation of the suspected prostate cancer site, is recommended.

5.2 Radiation Risks

Gallium Ga 68 Gozetotide Injection contributes to a patient's overall long-term cumulative radiation exposure. Long-term cumulative radiation exposure is associated with an increased risk for cancer. Ensure safe handling to minimize radiation exposure to the patient and health care workers. Advise patients to hydrate before and after administration and to void frequently after administration [see Dosage and Administration (2.1, 2.3)] .

6 ADVERSE REACTIONS

Clinical Trials Experience

Because clinical trials are conducted under widely varying conditions, adverse reaction rates observed in the clinical trials of a drug cannot be directly compared to rates in the clinical trials of another drug and may not reflect the rates observed in practice.

The safety of Gallium Ga 68 Gozetotide Injection was evaluated in 960 patients, each receiving one dose of Gallium Ga 68 Gozetotide Injection. The average injected activity was 188.7 ± 40.7 MBq (5.1 ± 1.1 mCi).

The most commonly reported adverse reactions were nausea, diarrhea, and dizziness, occurring at a rate of <1%

7 DRUG INTERACTIONS

Androgen deprivation therapy and other therapies targeting the androgen pathway

Androgen deprivation therapy (ADT) and other therapies targeting the androgen pathway, such as androgen receptor antagonists, can result in changes in uptake of gallium Ga 68 gozetotide in prostate cancer. The effect of these therapies on performance of gallium Ga 68 gozetotide PET has not been established.

8 USE IN SPECIFIC POPULATIONS

8.1 Pregnancy

Risk Summary

Gallium Ga 68 Gozetotide Injection is not indicated for use in females. There are no available data with Gallium Ga 68 Gozetotide Injection use in pregnant women to evaluate for a drug-associated risk of major birth defects, miscarriage, or adverse maternal or fetal outcomes. All radiopharmaceuticals, including Gallium Ga 68 Gozetotide Injection, have the potential to cause fetal harm depending on the fetal stage of development and the magnitude of the radiation dose. Animal reproduction studies have not been conducted with gallium Ga 68 gozetotide Injection.

8.2 Lactation

Risk Summary

Gallium Ga 68 Gozetotide Injection is not indicated for use in females. There are no data on the presence of gallium Ga 68 gozetotide in human milk, the effect on the breastfed infant, or the effect on milk production.

8.4 Pediatric Use

The safety and effectiveness of Gallium Ga 68 Gozetotide Injection have not been estabished in pediatric patients.

8.5 Geriatric Use

The efficacy of Gallium Ga 68 Gozetotide PET in geriatric patients with prostate cancer is based on data from two prospective studies [see Clinical Studies (14)] . Of the total number of subjects in these studies of Gallium Ga 68 Gozetotide Injection, 691 of 960 (72%) were 65 years of age and older.

The efficacy and safety profies of Gallium Ga 68 Gozetotide Injection appear similar in younger adult and geriatric patients with prostate cancer, althougth the number of younger adult patients in the trials was not large enought to allow definitive comparisons.

10 OVERDOSAGE

In the event of an overdose of Gallium Ga 68 Gozetotide Injection, reduce the radiation absorbed dose to the patient where possible by increasing the elimination of the drug from the body using hydration and frequent bladder voiding. A diuretic might also be considered. If possible, an estimate of the radiation effective dose given to the patient should be made.

11 DESCRIPTION

11.1 Chemical Characteristics

Gallium Ga Gozetotide Injection is a radioactive diagnostic agent for intravenous administration. It contains 0.5 mcg/mL Gozetotide, 18.5 MBq/mL to 185 MBq/mL (0.5 mCi/mL to 5 mCi/mL) of gallium Ga gozetotide at calibration time in 0.9% sodium chloride solution with not more than 10% ethanol (approximately 11 mL total volume). Gallium Ga Gozetotide Injection is provided as a sterile, pyrogen free, clear, colorless solution for intravenous use, with a pH between 4.0 and 7.0. Gozetotide is also known as PSMA-11.

Gallium Ga Gozetotide is a urea based peptidomimetic that has a covalently bound chelator (HBED-CC). The peptide has the amino acid sequence Glu-NH-CO-NH-Lys(Ahx)-HBED-CC. Gallium Ga Gozeotide has a molecular weight of 1011.91 g/mol and its chemical structure is shown in Figure 1.

Figure 1: Chemical Structure of Gallium Ga Gozetotide

11.2 Physical Characteristics

Gallium-68 (Ga 68) decays with a half-life of 68 minutes to stable zinc-68. Table 2 and Table 3 display the principle radiation emission data and physical decay of Ga 68.

Table 2: Principal Radiation Emission Data (>1%) for Gallium Ga 68
Radiation/ Emission | % Disintegration | Mean Energy (MeV)
beta+ | 88% | 0.8360
beta+ | 1.1% | 0.3526
gamma | 178% | 0.5110
gamma | 3.0% | 1.0770
X-ray | 2.8% | 0.0086
X-ray | 1.4% | 0.0086

Table 3: Physical Decay Chart for Gallium Ga 68
Minutes | Fraction Remaining
0 | 1
15 | 0.858
30 | 0.736
60 | 0.541
90 | 0.398
120 | 0.293
180 | 0.158
360 | 0.025

11.3 External Radiation

Table 4 displays the radiation attenuation by lead shielding of Ga 68.

Table 4: Radiation Attenuation of 511 keV Photons by Lead (Pb) Shielding
Shield Thickness (Pb) mm | Coefficient of Attenuation
6 | 0.5
12 | 0.25
17 | 0.1
34 | 0.01
51 | 0.001

12 CLINICAL PHARMACOLOGY

12.1 Mechanism of Action

Gallium Ga 68 gozetotode binds to prostate-specific membrane antigen (PSMA). It binds to cells that express PSMA, including malignant prostate cancer cells, which usually overexpress PSMA. Gallium-68 (Ga 68) is a β+ emitting radionuclide that allows positron emission tomography (PET).

12.2 Pharmacodynamics

The relationship between galium Ga 68 gozetotide plasma concentrations and successful imaging was not explored in clinical trials.

12.3 Pharmacokinetics

Distribution

Intravenously injected gallium Ga 68 gozetotide is cleared from the blood and is accumulated preferentially in the liver (15%), kidneys (7%), spleen (2%), and salivary glands (0.5%). Gallium Ga 68 gozetotide uptake is also seen in the adrenals and prostate. There is no uptake in the cerebral cortex or in the heart, and usually lung uptake is low.

Elimination

A total of 14% of the injected dose is excreted in urine in the first 2 hours post-injection.

13 NONCLINICAL TOXICOLOGY

13.1 Carcinogenesis, Mutagenesis, Impairment of Fertility

No long-term animal studies were performed to evaluate the carcinogenicity potential of gallium Ga 68 gozetotide.

14 CLINICAL STUDIES

The safety and efficacy of Gallium Ga 68 Gozetotide Injection were established in two prospective, open-label
studies, PSMA-PreRP (NCT03368547 and NCT02919111) and PSMA-BCR (NCT02940262 and
NCT02918357), in men with prostate cancer.

PSMA-PreRP

This two-center study enrolled 325 patients with biopsy-proven prostate cancer who were considered
candidates for prostatectomy and pelvic lymph node dissection. All enrolled patients met at least one of
the following criteria: serum prostate-specific antigen (PSA) of at least 10 ng/mL, tumor stage cT2b or
greater, or Gleason score greater than 6. Each patient received a single gallium Ga 68 gozetotide PET/CT
or PET/MR from mid-thigh to skull base.

A total of 123 patients (38%) proceeded to standard-of-care prostatectomy and template pelvic lymph
node dissection and had sufficient histopathology data for evaluation (evaluable patients). Three members
of a pool of six central readers independently interpreted each PET scan for the presence of abnormal
gallium Ga 68 gozetotide uptake in pelvic lymph nodes located in the common iliac, external iliac,
internal iliac, and obturator subregions bilaterally as well as in any other pelvic location. The readers were
blinded to all clinical information except for the history of prostate cancer prior to definitive treatment.
Extrapelvic sites and the prostate gland itself were not analyzed in this study. For each patient, gallium Ga
68 gozetotide PET results and reference standard histopathology obtained from dissected pelvic lymph
nodes were compared by region (left hemipelvis, right hemipelvis, and other).

For the 123 evaluable patients, the mean age was 65 years (range 45 to 76 years), and 89% were white.
The median serum PSA was 11.8 ng/mL. The summed Gleason score was 7 for 44%, 8 for 20%, and 9 for
31% of the patients, with the remainder of the patients having Gleason scores of 6 or 10.

Table 5 compares majority PET reads to pelvic lymph node histopathology results at the patient-level
with region matching, such that at least one true positive region defines a true positive patient. As shown,
approximately 24% of subjects studied were found to have pelvic nodal metastases based on
histopathology (95% confidence interval: 17%, 32%).

Table 5: Patient-Level Performance of Ga 68 PSMA-11 PET for Detection of Pelvic Lymph Node Metastasis [with region matching where at least one true positive region defines a true positive patient] in the PSMA-PreRP Study (n=123)
 |  | Histopathology |  | Predictive value (95% CI) [PPV: positive predictive value, NPV: negative predictive value]
 |  | Positive | Negative | Predictive value (95% CI) [PPV: positive predictive value, NPV: negative predictive value]
PET scan | Positive | 14 | 9 | PPV 61% (41%, 81%)
PET scan | Negative | 16 | 84 | NPV 84% (79%, 91%)
Total |  | 30 | 93
Diagnostic performance (95% CI) |  | Sensitivity 47% (29%, 65%) | Specificity 90% (84%, 96%)

Among the pool of six readers, sensitivity ranged from 36% to 60%, specificity from 83% to 96%, positive predictive value from 38% to 80%, and negative predictive value from 80% to 88%.

In an exploratory subgroup analysis based on summed Gleason score, there was a numerical trend toward more true positives in patients with Gleason score of 8 or higher compared to those with Gleason score of 7 or lower.

An exploratory analysis was performed to estimate the sensitivity and specificity for pelvic nodal metastasis detection in all scanned patients, including the patients who were lacking histopathology reference standard. An imputation method was used based on patient-specific factors. This exploratory analysis resulted in an imputed sensitivity of 47%, with a 95% confidence interval ranging from 38% to 55%, and an imputed specificity of 74%, with a 95% confidence interval ranging from 68% to 80% for all patients imaged with gallium Ga 68 gozetotide PET.

PSMA-BCR

This two-center study enrolled 635 patients with biochemical evidence of recurrent prostate cancer after definitive therapy, defined by serum PSA of >0.2 ng/mL more than 6 weeks after prostatectomy or by an increase in serum PSA of at least 2 ng/mL above nadir after definitive radiotherapy. All patients received a single gallium Ga 68 gozetotide PET/CT or PET/MR from mid-thigh to skull base. Three members of a pool of nine independent central readers evaluated each scan for the presence and regional location (20 subregions grouped into four regions) of abnormal gallium Ga 68 gozetotide uptake suggestive of recurrent prostate cancer. The readers were blinded to all clinical information other than type of primary therapy and most recent serum PSA level.

A total of 469 patients (74%) had at least one positive region detected by gallium Ga 68 gozetotide PET majority read. The distribution of gallium Ga 68 gozetotide PET positive regions was 34% bone, 25% prostate bed, 25% pelvic lymph node, and 17% extrapelvic soft tissue. Two hundred and ten patients had composite reference standard information collected in a PET positive region (evaluable patients), consisting of at least one of the following: histopathology, imaging (bone scintigraphy, CT, or MRI) acquired at baseline or within 12 months after gallium Ga 68 gozetotide PET, or serial serum PSA. Composite reference standard information for gallium Ga 68 gozetotide PET negative regions was not systematically collected in this study.

In the 210 evaluable patients, the mean age was 70 years (range 49 to 88 years) and 82% were 65 years of age or older. White patients made up 90% of the group. The median serum PSA was 3.6 ng/mL. Prior treatment included radical prostatectomy in 64% and radiotherapy in 73%.

Of the 210 evaluable patients, 192 patients (91%) were found to be true positive in one or more regions against the composite reference standard (95% confidence interval: 88%, 95%). Among the pool of nine readers used in the study, the proportion of patients who were true positive in one or more regions ranged from 82% to 97%. The prostate bed had the lowest proportion of true positive results at the region-level (76% versus 96% for non-prostate regions).

An exploratory analysis was also performed in which gallium Ga 68 gozetotide PET positive patients who lacked reference standard information were imputed using an estimated likelihood that at least one location-matched PET positive lesion was reference standard positive based on patient-specific factors. In this exploratory analysis, 340 of 475 patients (72%) were imputed as true positive in one or more regions (95% confidence interval: 68%, 76%).

In another exploratory analysis using the same imputation approach for PET positive patients who lacked reference standard information, 340 of 635 patients (54%) were correctly detected as true positive (95% confidence interval: 50%, 57%) among all BCR patients who received a PET scan, whether it was read as positive or negative.

The likelihood of identifying a gallium Ga 68 gozetotide PET positive lesion in this study generally increased with higher serum PSA level. Table 6 shows the patient-level gallium Ga 68 gozetotide PET results stratified by serum PSA level. The mean time between PSA measurement and PET scan was 40 days with a range of 0 to 367 days. Percent PET positivity was calculated as the proportion of patients with a positive gallium Ga 68 gozetotide PET out of all patients scanned. Percent PET positivity includes patients determined to be either true positive or false positive as well as those in whom such determination was not made due to the absence of composite reference standard data.

Table 6: Patient-Level gallium Ga 68 gozetotide PET Results and Percent PET Positivity Stratified by Serum PSA Level in the PSMA-BCR Study (n=628) [7 patients were excluded from this table due to protocol deviations]
PSA (ng/mL) | PET positive patients |  |  |  | PET negative patients | Percent PET positivity (95% CI) [Percent PET positivity = PET positive patients/total patients scanned]
PSA (ng/mL) | Total | TP [TP: true positive, FP: false positive] | FP‡ | Without reference standard
PSA (ng/mL) | Total | With reference standard
<0.5 | 48 | 11 | 1 | 36 | 87 | 36%
 |  | 12 |  |  |  | (27%, 44%)
0.5 and <1 | 44 | 15 | 3 | 26 | 35 | 56%
 |  | 18 |  |  |  | (45%, 67%)
1 and <2 | 71 | 29 | 1 | 41 | 15 | 83%
 |  | 30 |  |  |  | (75%, 91%)
2 | 299 | 137 | 13 | 149 | 29 | 91%
 |  | 150 |  |  |  | (88%, 94%)
Total | 462 | 192 | 18 | 252 | 166 | 74%
 |  | 210 |  |  |  | (70%, 77%)

16 HOW SUPPLIED/STORAGE AND HANDLING

How Supplied

Gallium Ga 68 Gozetotide Injection (NDC 24275-0525-1) is a clear, colorless solution, supplied in a capped glass vial containing 18.5 MBq/mL to 185 MBq/mL (0.5 mCi/mL to 5 mCi/mL) of gallium Ga 68 gozetotide at end of synthesis, in approximately 11 mL. The contents of each vial are sterile, pyrogen-free and preservative-free. The expiration date and time are provided on the container label. Use Gallium Ga 68 Gozetotide Injection within 4 hours of calibration time.

Storage and Handling

Storage

Store Gallium Ga 68 Gozetotide Injection upright in a lead shielded container at 25°C (77°F); excursions are permitted from 15°C to 30°C (59°F to 86°F). Store Gallium Ga 68 Gozetotide Injection within the original container in radiation shielding.

Handling

Receipt, transfer, handling, possession, or use of this product is subject to the radioactive material regulations and licensing requirements of the U.S. Nuclear Regulatory Commission, Agreement States, or Licensing States as appropriate.

17 PATIENT COUNSELING INFORMATION

Adequate Hydration

Instruct patients to drink a sufficient amount of water to ensure adequate hydration before their PET study and urge them to drink and urinate as often as possible during the first hours following the administration of Gallium Ga 68 Gozetotide Injection, in order to reduce radiation exposure [see Dosage and Administration (2.3) and Warnings and Precautions (5.2)] .

Manufactured and Distributed by:
University of California, San Francisco
UCSF Radiopharmaceutical Facility
185 Berry Street
Suite 350
San Francisco, CA 94107
415-353-4476

Drug Product Label

Vial and Radiation Shield